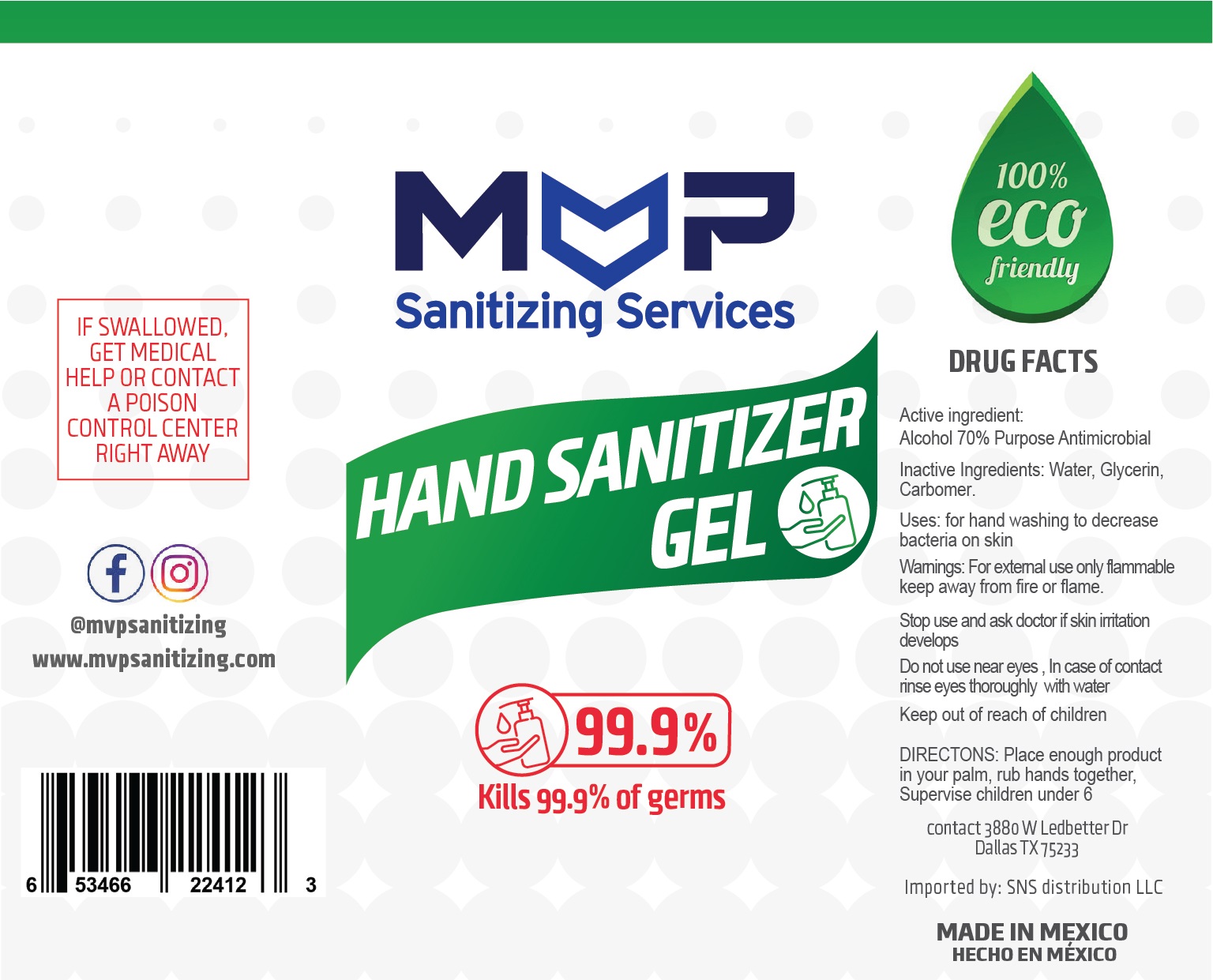 DRUG LABEL: Hand Sanitizer
NDC: 76947-199 | Form: GEL
Manufacturer: JOSE LOPEZ
Category: otc | Type: HUMAN OTC DRUG LABEL
Date: 20200702

ACTIVE INGREDIENTS: ALCOHOL 70 mL/100 mL
INACTIVE INGREDIENTS: GLYCERIN; CARBOMER 1342; WATER

HAND SANITIZER GEL

Active Ingredient(s)

Alcohol 70%

Purpose

Antimicrobial, Hand Sanitizer

Use

For hand washing to decrease bacteria on skin

Warnings

For external use only. Flammable. Keep away from fire or flame

Stop use and ask a doctor if skin irritation develops

Stop use and ask a doctor if irritation or rash occurs. These may be signs of a serious condition.

Keep out of reach of children. If swallowed, get medical help or contact a Poison Control Center right away.

Directions

- Place enough product on hands to cover all surfaces. Rub hands together until dry.
- Supervise children under 6 years of age when using this product to avoid swallowing.

Inactive ingredients

glycerin, water, carbomer

Package Label - Principal Display Panel

11000 mL NDC: 76947-199-28